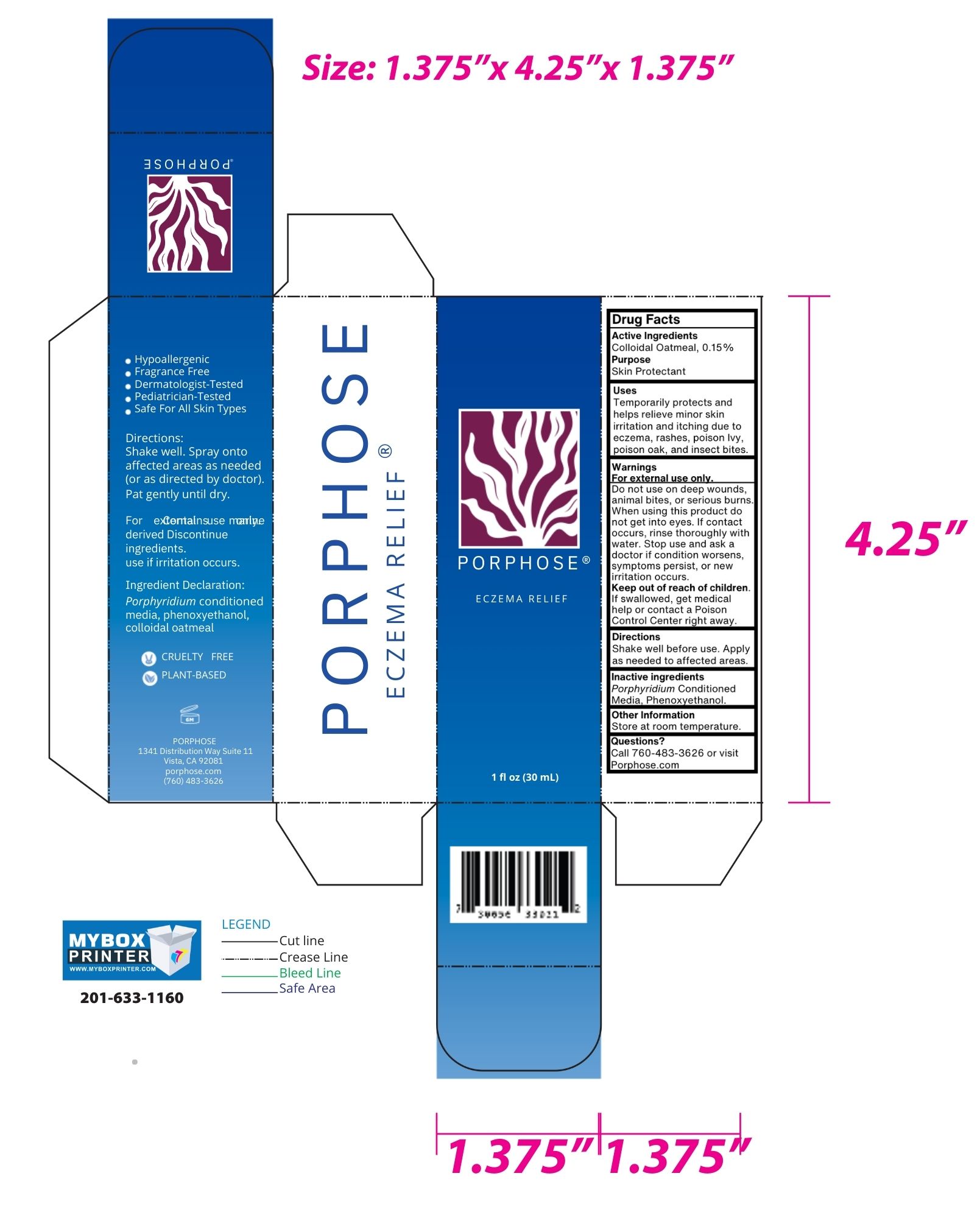 DRUG LABEL: Porphose
NDC: 85456-001 | Form: SPRAY
Manufacturer: Porphose
Category: otc | Type: HUMAN OTC DRUG LABEL
Date: 20250327

ACTIVE INGREDIENTS: OATMEAL 0.15 g/100 g
INACTIVE INGREDIENTS: PHENOXYETHANOL 1 g/100 g; PORPHYRIDIUM PURPUREUM 98.85 g/100 g

Active Ingredient

Active Ingredient: Colloidal Oatmeal 0.15%

Purpose of Active Ingredient

Purpose: Skin Protectan

Uses

Temporarily protects and helps relieve minor skin irritations and itching due to eczema, rashes, poison ivy, poison oak, poison sumac, and insect bites.

Warnings

For external use only. Do not use on deep wounds, animal bites, or serious burns. When using this product do not get into eyes. If contact occurs, rinse thoroughly with water. Stop use and ask a doctor if condition worsens, symptoms persist, or new irritation occurs.

Keep out of reach of children. If swallowed, get medical help or contact a Poison Control Center right away.

Directions

Shake well before use. Apply as needed to affected areas.

Other Information

Store at room temperature.

Inactive Ingredients

Porphyridium Conditioned Media, Phenoxyethanol.

Questions?

Call 760483-3626 or visit Porphose.com